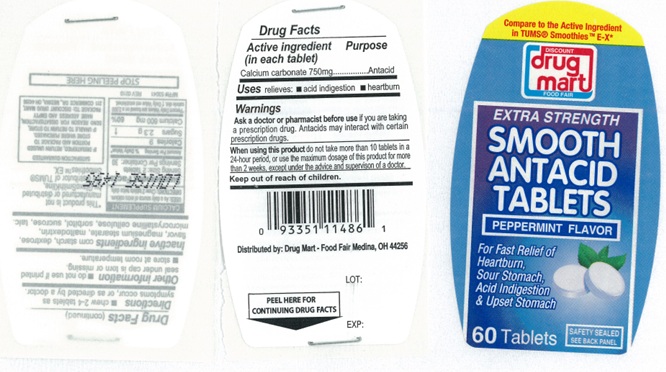 DRUG LABEL: Extra Strength Smooth Peppermint Antacid
NDC: 53943-180 | Form: TABLET, CHEWABLE
Manufacturer: Discount Drug Mart, Inc
Category: otc | Type: Human OTC Drug Label
Date: 20250220

ACTIVE INGREDIENTS: CALCIUM CARBONATE 750 mg/1 1
INACTIVE INGREDIENTS: STARCH, CORN; DEXTROSE, UNSPECIFIED FORM; MAGNESIUM STEARATE; MALTODEXTRIN; SUCROSE; TALC; SORBITOL; MICROCRYSTALLINE CELLULOSE

Extra Strength Smooth Antacid Peppermint Tablets

ACTIVE INGREDIENT (in each tablet)

Calcium carbonate 750 mg

PURPOSE

Antacid

USE(S)

relieves:

- acid indigestion
- heartburn

WARNINGS

.

ASK A DOCTOR OR PHARMACIST BEFORE USE IF YOU ARE

- taking a prescription drug. Antacids may interact with certain prescription drugs.

WHEN USING THIS PRODUCT

do not take more than 10 tablets in a 24-hour period, or use the maximum dosage of this product for more than 2 weeks, except under the advice and supervision of a doctor.

KEEP OUT OF REACH OF CHILDREN

.

DIRECTIONS

- adults and children 12 years of age and over: chew 2-4 tablets as symptoms occur, or as directed by a doctor.

OTHER INFORMATION

- do not use if printed seal under cap is torn or missing.
- store at room temperature.

INACTIVE INGREDIENTS

corn starch, dextrose, flavor, magnesium stearate, maltodextrin, microcrystalline cellulose, sorbitol, sucrose, talc.

PRINCIPAL DISPLAY PANEL

Compare to the Active Ingredient TUMS® SmoothiesTM E-X*

NDC 53943-180-23
DISCOUNT drug mart
FOOD FAIR

EXTRASTRENGTH
Smooth Antacid Tablets
PEPPERMINT FLAVOR
For Fast Relief of

Heartburn,

Sour Stomach,

Acid Indigestion

& Upset Stomach

60 Tablets